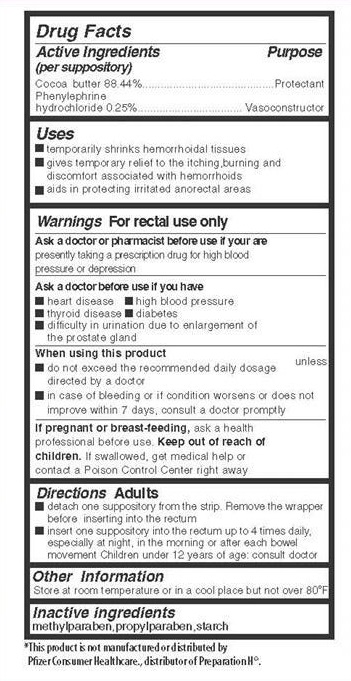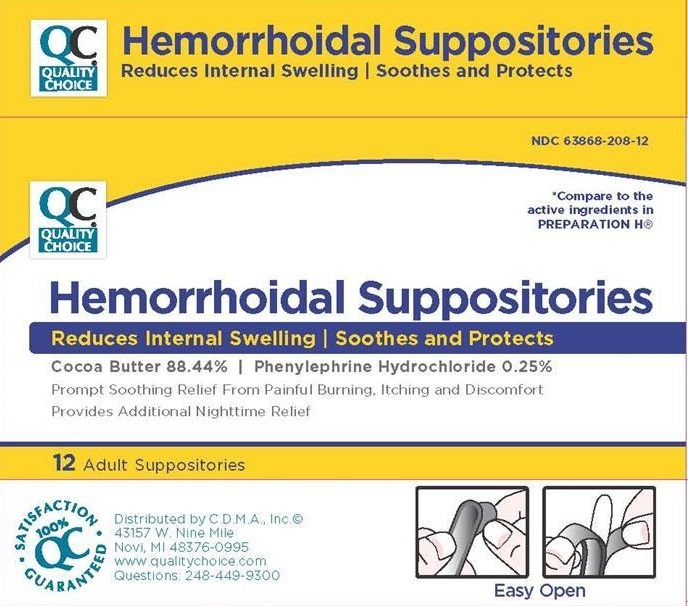 DRUG LABEL: Hemorrhoidal
NDC: 63868-208 | Form: SUPPOSITORY
Manufacturer: Chain Drug Marketing Association, Inc.
Category: otc | Type: HUMAN OTC DRUG LABEL
Date: 20210519

ACTIVE INGREDIENTS: COCOA BUTTER 1768.8 mg/1 1; PHENYLEPHRINE HYDROCHLORIDE 5 mg/1 1
INACTIVE INGREDIENTS: METHYLPARABEN; PROPYLPARABEN; STARCH, CORN

Chain Drug Marketing Association - Hemorrhoidal Suppository

Active Ingredients

(per suppository)
Cocoa butter 88.44 %
Phenylephrine hydrochloride 0.25 %

Purposes

Protectant
Vasoconstructor

Keep out of reach of children.
If swallowed, get medical help or contact a Poison Control Center right away.

Uses

- temporarily shrinks hemorrhoidal tissues
- gives temporary relief to the itching, burning and discomfort associated with hemorrhoids
- aids in protecting irritated anorectal areas

Warnings

For rectal use only

Ask a doctor or pharmacist before use if you are

presently taking a prescription drug for high blood pressure or depression

Ask a doctor before use if you have

- heart disease
- thyroid disease
- high blood pressure
- diabetes
- difficulty in urination due to enlargement of the prostate gland

When using this product

- do not exceed the recommended daily dosage unless directed by a doctor
- in case of bleeding or if condition worsens or does not improve within 7 days, consult a doctor promptly

If pregnant or breast-feeding

ask a health professional before use.

Directions Adults

- detach one suppository from the strip. Remove the wrapper before inserting into the rectum.
- insert one suppository into the rectum up to 4 times daily, especially at night, in the morning or after each bowel movement. Children under 12 years of age: consult doctor

Other Information

Store at room temperature or in a cool place but not over 80° F

Inactive ingredients

methylparaben, propylparaben, starch